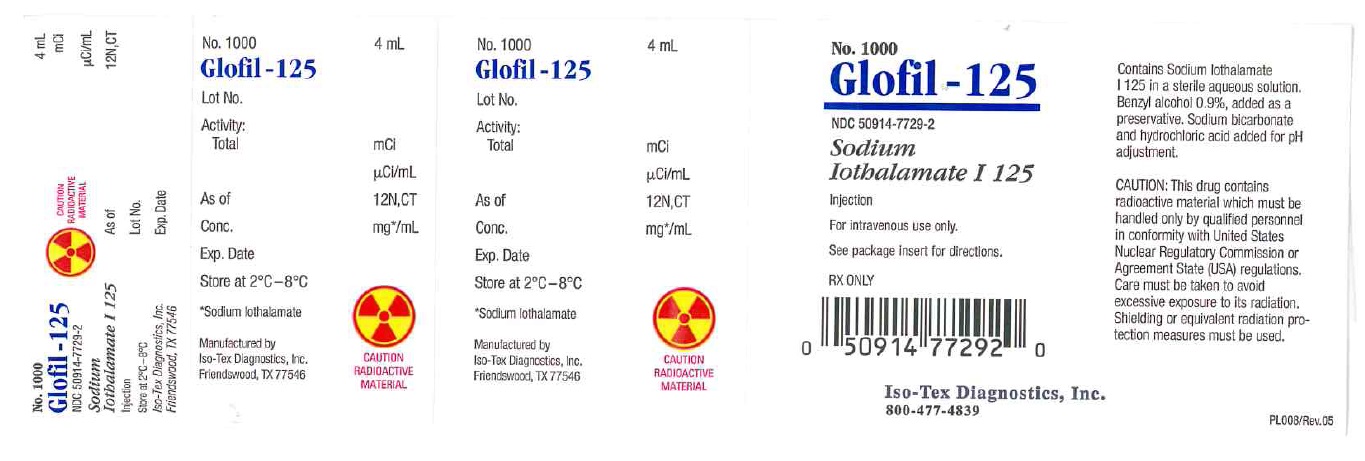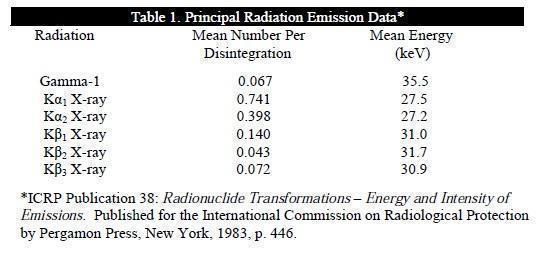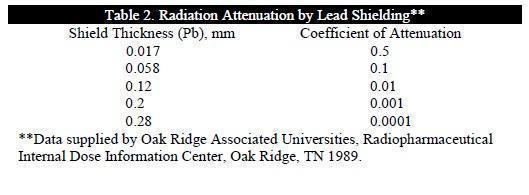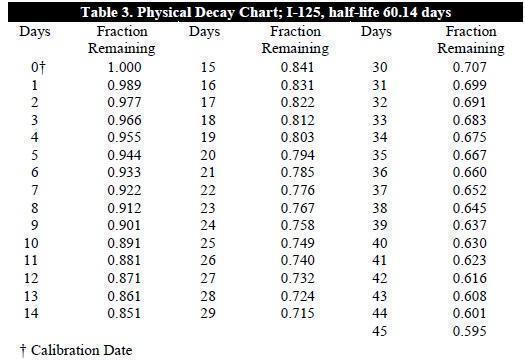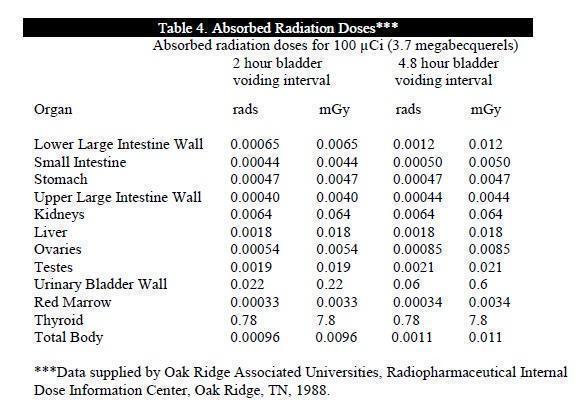 DRUG LABEL: Glofil-125
NDC: 50914-7729 | Form: INJECTION, SOLUTION
Manufacturer: Iso-Tex Diagnostics, Inc.
Category: prescription | Type: HUMAN PRESCRIPTION DRUG LABEL
Date: 20191209

ACTIVE INGREDIENTS: IOTHALAMATE SODIUM I-125 0.275 mCi/1 mL
INACTIVE INGREDIENTS: BENZYL ALCOHOL; SODIUM BICARBONATE; HYDROCHLORIC ACID

Glofil-125

Rx Only

DESCRIPTION

General
GLOFIL-125 (Sodium Iothalamate I-125 Injection) is a sterile, nonpyrogenic aqueous injection containing approximately 1 mg sodium iothalamate per mL, and 0.9 percent benzyl alcohol as a preservative. The radioactive concentration of the material is 250-300 µCi/mL as of the calibration date. Sodium bicarbonate and hydrochloric acid are present for pH adjustment.

Physical Characteristics

Iodine-125 decays by electron capture with a physical half-life of 60.14 days.

Photons that are useful for detection are listed in Table 1.

The specific gamma ray constant for I-125 is 1.43 R/mCi-hr at 1 cm. The first half value thickness of lead (Pb) for I-125 is 0.017 mm. A range of values for the relative attenuation of the radiation emitted by this radionuclide resulting from interposition of various thicknesses of Pb is shown in Table 2. For example, the use of 0.28 mm of Pb will decrease the external radiation exposure by a factor of 10,000.

To correct for physical decay of this radionuclide, the fractions that remain at selected time intervals after the date of calibration are shown in Table 3.

CLINICAL PHARMACOLOGY

The renal clearance of sodium iothalamate in man closely approximates that of inulin. The compound is cleared by glomerular filtration without tubular secretion or reabsorption. Following infusion administration of I-125 iothalamate, the effective half-life is about 0.07 days.

INDICATIONS AND USAGE

GLOFIL-125 (Sodium Iothalamate I-125 Injection) is indicated for evaluation of glomerular filtration in the diagnosis or monitoring of patients with renal disease.

CONTRAINDICATIONS

GLOFIL-125 should not be administered via a central venous line.

WARNINGS

None known

PRECAUTIONS

General

As in the use of any radioactive material, care should be taken to minimize radiation exposure to the patient, consistent with proper patient management, and to insure minimum radiation exposure to occupational workers. Radiopharmaceuticals should be used only by physicians who are qualified by training and experience in the safe use and handling of radionuclides. Rapid or bolus-like injections should be avoided.

Carcinogenesis, Mutagenesis, Impairment of Fertility

No long-term animal studies have been performed to evaluate carcinogenic potential, mutagenic potential, or whether this drug affects fertility in males or females.

Pregnancy Category C

Animal reproduction studies have not been conducted with GLOFIL-125. It is also not known whether GLOFIL-125 can cause fetal harm when administered to a pregnant woman or can affect reproduction capacity. GLOFIL-125 should be given to a pregnant woman only if clearly needed.

Nursing Mothers

Radioiodine is excreted in human milk during lactation. It is not known whether GLOFIL-125 is excreted in human milk. Therefore, formula feedings should be substituted for breast feedings.

Pediatric Use

Safety and effectiveness in children have not been established.

ADVERSE REACTIONS

None Reported

Dosage

The suggested dose range employed in the average patient (70 kg) is as follows:

Continuous intravenous infusion: 20 to 100 μCi (0.74-3.7 megabecquerels) (Sigman, et al (1) method).

Single intravenous injection: 10 to 30 µCi (0.37-1.11 megabecquerels) Cohen, et al (2) method)

The patient dose should be measured by a suitable radioactivity calibration system immediately prior to administration.

Technique
Continuous intravenous infusion

Sigman^1 method

I. Preparation:

1. Adequate diuresis (a urine flow exceeding 3 mL/min.) is established, preferably by an oral water load of 1,500 mL two hours prior to the beginning of the clearance study.

2. It is not necessary to withhold breakfast or admit the patient the night before.

II. Procedure:

1. After the establishment of adequate diuresis, a number 14 or 16 French Foley catheter is aseptically inserted into the bladder.
2. An intravenous infusion of Lactated Ringers (Hartmanns) solution is started in each arm, one to maintain a site for injection of the GLOFIL-125, the other to serve as a site for serial withdrawal of blood. A two-way stopcock connects the needle and intravenous tubing of each arm.
3. The dose is equally divided into (1) an intravenous priming dose to be injected as is and (2) a sustaining dose to be diluted in 30 to 60 mL of isotonic sodium chloride, depending on how many collection periods are anticipated.
4. The priming dose is slowly injected into one arm. This is immediately followed by infusion of the sustaining solution through the same site, usually at the rate of 0.5 mL/min., by means of an automatic pump. During this infusion, the Lactated Ringers solution in the same arm is discontinued, and 40 to 45 minutes are allowed for equilibration in order to reach a state of constant plasma concentration of radioactivity.
5. After attaining equilibrium, consecutive 15 minute collection periods are started. From the arm opposite the injection site, 5 mL of blood (allowing duplicate plasma counting volumes) is drawn six minutes prior to the midpoint of each collection period, placed in heparinized tubes, mixed, and centrifuged. The blood samples may be obtained through the two-way stopcock after discarding the first 30 mL aspirated into the syringe. This 30 mL contains the contents of the tubing, including infusion fluid, and must be cleared in order to obtain an undiluted blood sample. If desired, this step may be eliminated and blood samples obtained by direct venipuncture.
6. During each collection period, total urine must be accurately collected and the volume accurately measured. Three such consecutive collection periods are sufficient for most clinical studies.

III. Clearance Calculations:

1. Aliquots (1 mL each) of plasma and urine from each collection period are counted in a standard gamma-ray scintillation well detector.

2. All counts are corrected for background activity.

3. Glomerular filtration rate is calculated by the formula C=UV/P, in which:

C = glomerular filtration rate in mL/min
U= urinary concentration of radioactivity in net counts/min/mL
V= urinary flow rate in mL/min
P = plasma concentration of radioactivity in net counts/min/mL

4. Average glomerular filtration rate (GFR) is calculated from the rates for the individual collection periods. GFR can be expressed in terms of body

weight (mL/min/kg) or body surface area (mL/min/m^2).

5. Unilateral glomerular filtration rates can be determined by the same technique by utilizing ureteral catheterization.

Single intravenous injection

Cohen^2 method:

The method of Cohen, et al^2 requires little preparation, few and small blood samples, no bladder catheterization, and no constant intravenous infusion. It is simple to perform, rapid, and utilizes equipment which is readily available in most modern laboratories.

I. Preparation:

1. Lugol's solution, 3 drops orally, three times a day, is administered for one or two days prior to the test.

No diet or water restriction is necessary.

2. Oral water load is begun one hour before starting the test. Start with 20 mL/kg and force any clear liquids (unless contraindicated) until the test is complete.

II. Procedure: Record actual times for the collection of the blood and urine samples.

1. Empty the bladder and label the urine Urine control.

2. Inject 10-30 µCi GLOFIL-125 intravenously; wait 30 to 60 minutes.

3. Collect the entire urine and label Urine discard.

4. Draw 4 to 5 mL of blood into a heparinized syringe. Label Plasma #1.

5. After another 30 to 60 minutes, collect the entire urine and label Urine #1.

6. Immediately draw another blood specimen. Label Plasma #2.

7. After final 30 to 60 minute wait, collect the urine. Label Urine #2.

8. Draw the last blood specimen immediately. Label Plasma #3.

III. Clearance Calculations:

1. Radioactivity of one mL aliquots of both urine and plasma are determined using a well-scintillation detector with a single channel pulse-height analyzer. Sufficiently reproducible counts are usually obtained with time settings of 2 minutes for urine samples and 20 minutes for the plasma samples. Calculations of the clearance rates are made by using the formula:(1)

C = C = UV/P + 1.73/SA where

C = glomerular filtration rate in mL/min/1.73 m^2

U = urine radioactivity in counts/min/mL

V = urine flow rate in mL/min

P= mean plasma radioactivity in counts/min/mL

SA= body surface area in m^2

Radiation Dosimetry
The estimated absorbed radiation doses to an average (70 kg) patient from an intravenous dose of 100 µCi (3.7 megabecquerels) of GLOFIL-125 are shown in Table 4. Calculations assume that there is 1% free iodide in the preparation and that the thyroid uptake of the iodine is 25%.

Visual Inspection

Parental drug products should be inspected visually for particulate matter and discoloration prior to admnistration, whenever solution and container permit.

HOW SUPPLIED

Identity

No. 1000, GLOFIL-125 is a clear, colorless, sterile, and nonpyrogenic solution available as a 4 mL vial. It is supplied in a concentration of approximately 1 mg/mL sodium iothalamate (range is 0.5–2.0 mg sodium iothalamate per mL), with a radioactivity concentration of 250 to 300 μCi/mL at the time of calibration. Benzyl alcohol 0.9%, is added as a preservative. Sodium bicarbonate and hydrochloric acid are added for pH adjustment. The calibration and expiration dates are shown on the label.

Storage

Refrigerate the product upon receipt at 2°C to 8°C.

Dose Volume Calculation

Table 3 provides the required factors for the determination of activity per mL post calibration date for GLOFIL-125 sterile solution.

To determine the dose volume, locate the decay factor (fraction remaining) which corresponds to the day that the dose is to be administered. The following equation is then utilized to determine the dose volume:

activity of desired dose = dose

decay factor x amount of activity/mL on calibration day volume (mL)

(information on label)

REFERENCES

1. Sigman EM, Elmwood CM, Reagan ME, Morris AM, Calanzaro A. The renal clearance of ^131 I labeled sodium iothalamate in man. Invest Urol 1965; 2:432.

2. Cohen ML, Smith FG Jr., Mindell RS, Vernier RL. A simple reliable method of measuring glomerular filtration rate using single low dose sodium iothalamate ^131I. Pediatrics 1969; 43:407

ADDITIONAL REFERENCES

3. Maher FT, Nolan NG, Elveback LR. Comparisons of simultaneous clearances of ^125I labeled sodium iothalamate (Glofil) and of Inulin. Mayo Clin Proc 1971; 46: 690-691.

4. Skov PE. Glomerular filtration rate in patients with severe and very severe renal insufficiency. Acta Med Scand 1970; 187:419-428.

Manufactured by Iso-Tex Diagnostics, Inc.

Iso-Tex Diagnostics, Inc.
Friendswood, TX 77546
800-477-4839